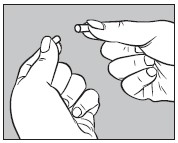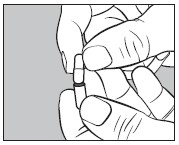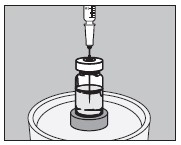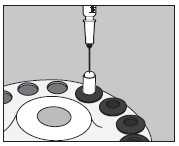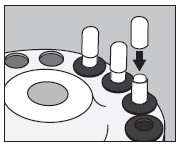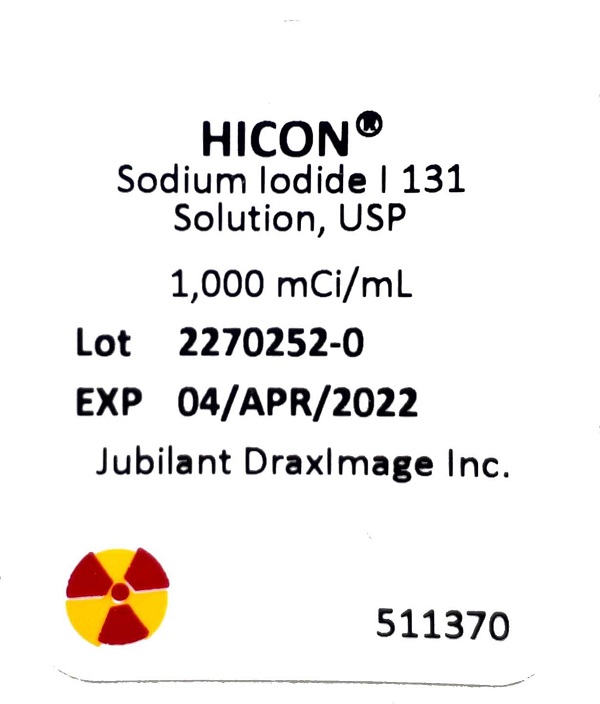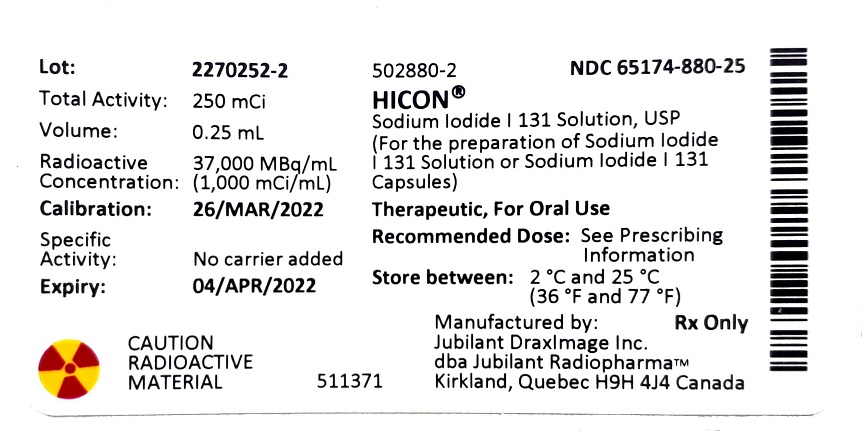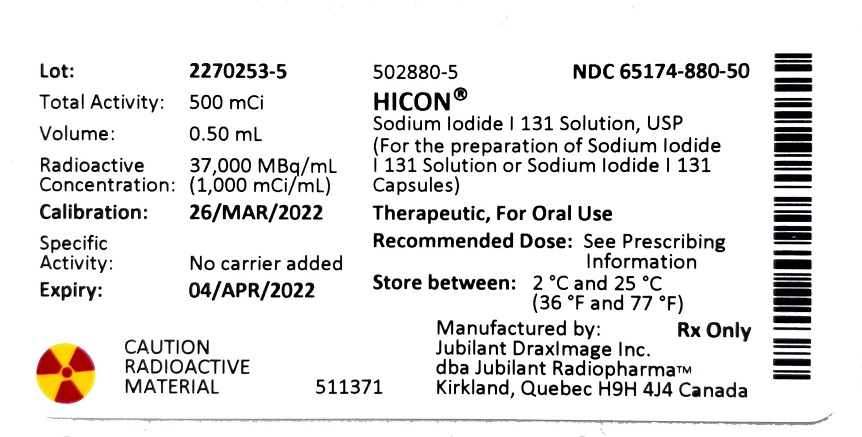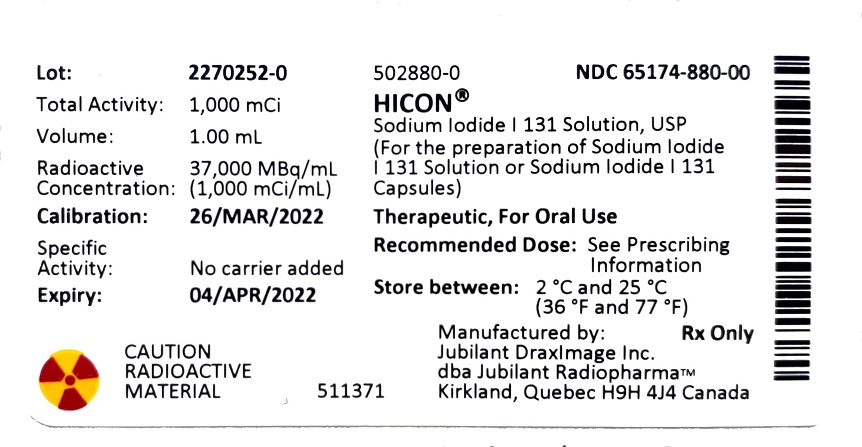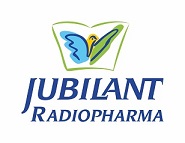 DRUG LABEL: HICON 
NDC: 65174-880 | Form: SOLUTION
Manufacturer: Jubilant DraxImage Inc., dba Jubilant Radiopharma
Category: prescription | Type: Human Prescription Drug Label
Date: 20250121

ACTIVE INGREDIENTS: SODIUM IODIDE I-131 1000 mCi/1 mL
INACTIVE INGREDIENTS: Edetate Disodium; Sodium Thiosulfate; SODIUM PHOSPHATE, DIBASIC, ANHYDROUS

HIGHLIGHTS OF PRESCRIBING INFORMATION

These highlights do not include all the information needed to use HICON® safely and effectively. See full prescribing information for HICON®.
HICON® (for the preparation of sodium iodide I 131 solution or sodium iodide I 131 capsules), therapeutic, for oral use.
Initial U.S. Approval: 1971

RECENT MAJOR CHANGES

Dosage and Administration (2) 06/2021

Contraindications (4) 06/2021

Warnings and Precautions (5) 06/2021

1 INDICATIONS AND USAGE

HICON® is a radioactive therapeutic agent indicated for the treatment of hyperthyroidism and selected cases of carcinoma of the thyroid.

2 DOSAGE AND ADMINISTRATION

- The concentrated sodium iodide I 131 solution USP provided with HICON® must be diluted. (2.2)
- See Full Prescribing Information for important administration instructions and dilution and preparation instructions for sodium iodide l 131 capsules or oral solution. (2.2, 2.4)
- The recommended dose is based on the thyroid gland uptake as well as the size of the gland:
  - Treatment of Hyperthyroidism: Recommended dosage is 148 MBq to 370 MBq (4 mCi to 10 mCi). (2.3)
  - Treatment of Thyroid Carcinoma: Recommended dosage is 1,110 MBq to 3,700 MBq (30 mCi to 100 mCi). (2.3)

3 DOSAGE FORMS AND STRENGTHS

Vials: Sodium Iodide I 131 Solution [9,250 MBq (250 mCi), 18,500 MBq (500 mCi), and 37,000 MBq (1,000 mCi) at time of calibration] for the preparation of sodium iodide I 131 capsules, therapeutic or sodium iodide I 131 solution, therapeutic.

4 CONTRAINDICATIONS

- Patients with vomiting and diarrhea. (4)
- Patients with thyroid malignancies shown to have no iodide uptake. (4)
- Patients receiving concurrent anti-thyroid therapy. (4)
- Pregnancy. (4)
- Lactation. (4)

5 WARNINGS AND PRECAUTIONS

- Radiation-induced thyroiditis may cause or worsen hyperthyroidism. Consider pre-treatment with anti-thyroid medications. (5.1)
- Multiple non-thyroid radiation toxicities, including hematopoietic suppression: Individualize dose and monitor for toxicity. (5.2)
- Embryo-Fetal toxicity: May cause severe and irreversible hypothyroidism in the neonate. Verify pregnancy status in females of reproductive potential prior to initiating treatment. Females and males of reproductive potential should use effective contraception. (5.4, 8.1, 8.3)
- Radiation exposure to breast tissue with lactation: Sodium iodide I 131 concentrates in the breast of lactating women. Discontinue breast feeding at least 6 weeks prior to therapy. (5.5, 8.2)

6 ADVERSE REACTIONS

Common adverse reactions reported with therapeutic doses of sodium iodide I 131 include local swelling, radiation sickness, sialadenitis, salivary gland dysfunction, bone marrow depression, lacrimal gland dysfunction, hypothyroidism, hyperthyroidism, thyrotoxic crisis. (6)

To report SUSPECTED ADVERSE REACTIONS, contact Jubilant DraxImage Inc., dba Jubilant RadiopharmaTM at 1-888-633-5343 or FDA at 1-800-FDA-1088 or www.fda.gov/medwatch.

7 DRUG INTERACTIONS

Many pharmacologic agents are known to interact with radioiodide. See Full Prescribing Information complete list. (5.8, 7)

8 USE IN SPECIFIC POPULATIONS

- Pregnancy. (4)
- Lactation. (4)
- Females and Males of Reproductive Potential: May impair fertility in females and males. (5.6, 8.3)

FULL PRESCRIBING INFORMATION

1 INDICATIONS AND USAGE

HICON® is indicated for the treatment of hyperthyroidism and selected cases of thyroid carcinoma.

2 DOSAGE AND ADMINISTRATION

2.1 Radiation Safety

- HICON® is a radioactive drug. Handle with appropriate safety measures to minimize radiation exposure to the patient and healthcare workers [see Warnings and Precautions (5.7)]:
  - Use only by, or under the direction of, physicians who are qualified by specific training and experience in the safe use and handling of radioactive materials, and whose experience and training have been approved by the appropriate governmental agency authorized to license the use of radiopharmaceuticals.
  - Use waterproof gloves when handling and administering the product.
  - Maintain adequate shielding during the life of the product.
  - Measure patient dose with a suitable radioactivity calibration system immediately prior to administration.

2.2 Important Administration Instructions

- Do not directly administer the concentrated sodium iodide I 131 solution USP provided with HICON® to patients. The concentrated sodium iodide I 131 solution USP must be diluted and prepared prior to administration [see Dosage and Administration (2.4)].
- Obtain a pregnancy test in females of reproductive potential prior to administration to verify the absence of pregnancy [see Contraindications (4) and Use in Specific Populations (8.1, 8.3)].
- Instruct patients to fast at least 2 hours before and 2 hours after administration to ensure absorption.
- Instruct patients to hydrate before and after administration of sodium iodide I 131 and to void frequently to enhance urinary elimination of the radioiodide that is not absorbed by the thyroid gland [see Warnings and Precautions (5.2)].
- Instruct patients to maintain a low-iodide diet two weeks prior to radioiodide administration and continue for several days during the uptake or imaging process [see Warnings and Precautions (5.8) and Drug Interactions (7)].
- Instruct patients to discontinue the anti-thyroid therapy three days before administration of sodium iodide I 131 [see Warnings and Precautions (5.8) and Drug Interactions (7)].
- For patients with a history of renal impairment, evaluate renal function for therapeutic planning and consider dosimetry [see Use in Specific Populations (8.6)].
- Obtain a complete blood count within one month of therapy. If patients show leukopenia or thrombocytopenia, dosimetry should be used to determine a safe sodium iodide I 131 activity, while delivering less than 2 Gy to the bone marrow [see Warnings and Precautions (5.2)].

2.3 Recommended Dosage and Administration

Individualization of Therapy
The recommended dose for orally administered sodium iodide I 131 capsules or solution is based on the thyroid gland uptake as well as the size of the gland. Thyroidal uptake and size should be determined by the physician prior to treatment and may be useful in calculating the therapeutic dose to be administered to the individual patient.

Treatment of Hyperthyroidism
The recommended dose is 148 MBq to 370 MBq (4 mCi to 10 mCi) administered orally. Toxic nodular goiter may require a larger dose.

Treatment of Thyroid Carcinoma
The recommended dose is 1,100 MBq to 3,700 MBq (30 mCi to 100 mCi) administered orally. For subsequent ablation of metastases, the recommended dose is 3,700 MBq to 7,400 MBq (100 mCi to 200 mCi) administered orally.

2.4 Dilution and Preparation Instructions

Drug Handling

1. Wear waterproof gloves throughout the entire handling and administration procedure.
2. Make all transfers of radioactive solutions with an adequately shielded syringe or remote handling equipment and maintain adequate shielding around the vial during the useful life of the radioactive product.

Preparation of Dilute Sodium Iodide I 131 Solution

1. Using the calibration date and radionuclide concentration on the label of the product vial, calculate the required volume to produce the necessary dose in MBq or mCi.
2. Using a shielded syringe, remove the required volume.
3. Using the shielded syringe, transfer the required volume to a suitably shielded receiving vial.
4. Add the solution diluent to the receiving vial to produce a final dose of the desired volume.
5. The recommended diluent is Purified Water USP containing 0.2% sodium thiosulfate USP as a reducing agent. Acidic diluents should not be used as they may cause the pH to drop below 7.5 and stimulate the volatilization of Iodine I 131 hydriodic acid.
6. Present the dose in a shielded container for administration to the patient with a straw.

Preparation of Sodium Iodide I 131 Capsules

1. HICON® includes one LARGE gelatin capsule and one SMALL gelatin capsule for each dose prepared. Each LARGE capsule is empty, and each SMALL capsule contains approximately 300 mg of dibasic sodium phosphate anhydrous USP as the absorbing buffer.
2. Using the calibration date and radionuclide concentration on the label of the product vial, calculate the required volume to produce the necessary dose in MBq or mCi.
3. Open one LARGE capsule supplied with HICON® by pulling apart the capsule into two pieces as illustrated below:
4. Insert an unopened SMALL capsule supplied with HICON® into the bottom half of the empty LARGE capsule as illustrated below:
5. With an appropriate syringe, withdraw the required volume of sodium iodide I 131 solution USP (maximum 150 microliters) from the vial as illustrated below:
6. Inject into the center of the SMALL capsule through the top as illustrated below and wait for 30 seconds to allow the solution to be absorbed by the absorbing buffer:
7. Slip the upper half of the LARGE capsule over the bottom half to completely cover the SMALL capsule and push down gently until locked as illustrated below:
8. Measure the patient dose in a suitable radioactivity calibration system immediately prior to administration.
9. Prepared capsules may be stored in a suitable polypropylene container and placed inside a lead pot until use, within seven days.

2.5 Radiation Dosimetry

- The biokinetic modeling and radiation dose distributions associated with thyroid uptake of iodide I 131 depend on dietary intake of stable iodide and presume normal production of thyroid hormone. Table 1 shows a range of uptake percentages in an average adult (73.7 kg reference model). Table 1 is not intended to be used for treatment planning.
- For a thyroid blocked from iodide uptake in the production of hormones, the effective half-life of iodide I 131 is approximately 1.4 hours; for “low” to “high” uptake, the effective half-life of I 131 ranges from approximately 80 hours to 90 hours.

Table 1 [Table 1 is not intended for treatment planning.] - Absorbed dose per unit activity sodium iodide I 131 administered orally (mGy/MBq) in adult (73.7 kg reference model)
Organ | Thyroid uptake of I 131 (% administered activity A0) 24 h after oral administration
Organ | Blocked thyroid (0% A0) | Low uptake [These columns are not applicable to estimate organ or effective doses in patients following thyroidectomy. In patients with thyroid cancer following thyroidectomy, organ and effective doses can be estimated from the "blocked"-thyroid-uptake values.] (16% A0) | Medium uptake (26% A0) | High uptake (36% A0)
Adrenals | 0.044 | 0.051 | 0.055 | 0.059
Bone surfaces | 0.03 | 0.089 | 0.12 | 0.16
Brain | 0.021 | 0.093 | 0.13 | 0.17
Breast | 0.02 | 0.038 | 0.048 | 0.058
Gallbladder wall | 0.037 | 0.043 | 0.046 | 0.049
Gastrointestinal tract
Esophagus | 0.024 | 0.1 | 0.14 | 0.19
Stomach wall | 0.87 | 0.77 | 0.71 | 0.66
Small intestine wall | 0.035 | 0.033 | 0.032 | 0.032
Colon wall | 0.14 | 0.14 | 0.14 | 0.14
(Upper large intestine wall) | 0.12 | 0.12 | 0.12 | 0.12
(Lower large intestine wall) | 0.17 | 0.17 | 0.17 | 0.16
Heart wall | 0.062 | 0.089 | 0.1 | 0.12
Kidneys | 0.27 | 0.27 | 0.27 | 0.27
Liver | 0.05 | 0.093 | 0.12 | 0.14
Lungs | 0.053 | 0.1 | 0.13 | 0.15
Muscles | 0.026 | 0.084 | 0.12 | 0.15
Ovaries | 0.038 | 0.037 | 0.036 | 0.035
Pancreas | 0.06 | 0.064 | 0.066 | 0.068
Red marrow | 0.031 | 0.072 | 0.095 | 0.12
Salivary glands | 0.27 | 0.22 | 0.19 | 0.16
Skin | 0.019 | 0.043 | 0.057 | 0.071
Spleen | 0.064 | 0.069 | 0.072 | 0.075
Testes | 0.025 | 0.024 | 0.023 | 0.22
Thymus | 0.024 | 0.1 | 0.14 | 0.19
Thyroid | 2.2 | 280 [These values presume unimpeded production of thyroid hormone and may not be applicable to estimate thyroid dose and effective dose in patients who have had previous treatment with I 131 for hyperthyroidism.] | 430 | 580
Urinary bladder wall | 0.54 | 0.45 | 0.39 | 0.34
Uterus | 0.045 | 0.042 | 0.04 | 0.038
Remaining organs | 0.029 | 0.084 | 0.11 | 0.15
Effective dose per administered activity (mSv/MBq) | 0.28 | 14 | 22 | 29

3 DOSAGE FORMS AND STRENGTHS

HICON® is available in 1 mL size, clear vials containing a colorless, aqueous, concentrated Sodium Iodide I 131 Solution USP [9,250 MBq (250 mCi), 18,500 MBq (500 mCi), and 37,000 MBq (1,000 mCi) at time of calibration] for the preparation of sodium iodide I 131 capsules, therapeutic or sodium iodide I 131 solution, therapeutic. Refer to Table 2 for the radioactivity and volume in each vial. Large gelatin capsules (empty) and small gelatin capsules containing approximately 300 mg of dibasic sodium phosphate anhydrous as the absorbing buffer are supplied along with HICON® for the preparation of sodium iodide I 131 capsules, therapeutic.

Table 2 HICON® Concentrated Sodium Iodide I 131 Solution USP
Total Radioactivity [At time of calibration] / Vial | Solution Volume (mL) / Vial
9,250 MBq (250 mCi) | 0.25
18,500 MBq (500 mCi) | 0.5
37,000 MBq (1,000 mCi) | 1

4 CONTRAINDICATIONS

HICON® is contraindicated in:

- Patients with vomiting and diarrhea [see Warnings and Precautions (5.7)].
- Patients with thyroid malignancies shown to have no iodide update, which include the majority of medullary or anaplastic carcinomas.
- Patients receiving concurrent anti-thyroid therapy [see Warnings and Precautions (5.1) and Drug Interactions (7)].
- Pregnancy [see Warnings and Precautions (5.4), Use in Specific Populations (8.1)].
- Lactation [see Warnings and Precautions (5.5), Use in Specific Populations (8.2)].

5 WARNINGS AND PRECAUTIONS

5.1 Radiation-induced Thyroiditis

Sodium iodide I 131 may cause thyroiditis with gland enlargement and release of thyroid hormone, which may cause or aggravate hyperthyroidism, thyroid storm and thyrotoxic cardiac disease [see Adverse Reactions (6)]. When treating hyperthyroidism, consider pre-treatment anti-thyroid medication to help deplete the thyroid hormone content within the gland. Discontinue the anti-thyroid medication at least three days before administration of sodium iodide I 131 [see Drug Interactions (7)]. Consider a beta-blocker pre or post-treatment to minimize the risk of hyperthyroidism and thyroid storm.

Thyroiditis may cause gland enlargement resulting in tenderness and swelling of the neck, pain on swallowing, sore throat, and cough; which may occur approximately the third day after sodium iodide I 131 administration. Consider management with pain-reliever or anti-inflammatory medications.

5.2 Radiation-induced Toxicities

Sodium Iodide I 131 may cause radiation induced toxicities [see Adverse Reactions (6)]:

- Dose-dependent fatalities (bone marrow suppression, malignancy).
- Dose-dependent hematopoietic suppression which manifests as a transient thrombocytopenia or neutropenia 3 to 5 weeks following sodium iodide I 131 administrations, may lead to increased susceptibility to infections or bleeding.
- Salivary gland toxicity: sialadenitis, xerostomia.
- Lacrimal gland toxicity: conjunctivitis, xerophthalmia, and epiphora.
- Increased risk of developing new solid tumors and leukemias.

Obtain a complete blood count within one month of therapy. If patients show leukopenia or thrombocytopenia, dosimetry should be used to determine a safe sodium iodide I 131 activity, while delivering less than 2 Gy to the bone marrow.

Advise good hydration for one week following sodium iodide I 131 administration and stimulate salivary flow via a sialagogue (e.g. sugar-free candy or gum, pilocarpine, and ascorbic acid) to reduce radiation exposure to the salivary glands.

Advise patients to void frequently after administration of radioiodide to enhance excretion.

5.3 Hypersensitivity Reactions

Hypersensitivity reactions including anaphylaxis may occur in patients who receive sodium iodide I 131. Although iodide is not considered an allergen, hypersensitivity reactions may occur in relation with excipients or chemical component of the capsule, such as sodium thiosulfate. Obtain and document an allergy history, particularly a sulfite allergy. Emergency resuscitation equipment and personnel should be immediately available [see Adverse Reactions (6)].

5.4 Embryo-Fetal Toxicity

HICON® is contraindicated in pregnancy because sodium iodide I 131 crosses the placenta and fetal exposure can lead to neonatal hypothyroidism. Multiple reports in the published literature describe hypothyroidism in the neonates following in utero exposure to sodium iodide I 131. Some cases of neonatal hypothyroidism were severe and irreversible. Verify pregnancy status of females of reproductive potential prior to initiating HICON® treatment. Advise females and males of reproductive potential to use effective contraception during treatment with HICON® and for at least 6 months after the last dose [see Use in Specific Populations (8.1, 8.3)].

5.5 Increased Radiation Exposure to Breast Tissue with Lactation

HICON® is contraindicated in lactating women because sodium iodide I 131 concentrates in the breast via the increased expression of the sodium iodide symporter in breast tissue with lactation. The literature describes moderate to marked radioiodine uptake in the breast tissue for 5 to 32 weeks post cessation of breast feeding. Advise lactating women to discontinue breast feeding at least 6 weeks prior to administration of sodium iodide I 131 to allow sufficient time for involution to occur and to avoid excess concentration of sodium iodide I 131 in breast tissue. Consider administration of drugs to suppress lactation. Consider diagnostic scintigraphy before administration of sodium iodide I 131 to assess the persistence of uptake by breast tissue. If sodium iodide I 131 is administered in the postpartum period, the lactating mother should not breastfeed the infant [see Use in Specific Populations (8.2)].

5.6 Transient Infertility

Transient dose-related impairment of testicular function in men and transient ovarian insufficiency in women has been reported after sodium iodide I 131 therapy. Sperm banking for men may be considered prior to administration of HICON® for thyroid carcinoma [see Use in Specific Populations (8.3)].

5.7 Radiation Exposure to Other Individuals

Household Contacts
Instruct patients to follow radiation safety precautions after receiving HICON® to minimize the radiation contamination of other persons or the environment. Patients should avoid close contact with others, especially pregnant women and children, and take care to avoid contamination of other persons or the environment with body fluids.

Patients and Healthcare Providers
HICON® contributes to a patient’s overall long-term cumulative radiation exposure, which is associated with an increased risk of cancer. Follow safe handling and administration to minimize radiation exposure to the patient and healthcare providers.

5.8 Risk of Decreased Effectiveness of Therapy

Certain food or drugs may alter the thyroid uptake of sodium iodide I 131 and diminish its effectiveness. Recent intake of stable iodide in any form, or the use of thyroid or anti-thyroid drugs may diminish thyroid uptake of sodium iodide I 131 [see Drug Interactions (7)].

6 ADVERSE REACTIONS

The following clinically significant adverse reactions are described below and elsewhere in labeling:

- Radiation-induced Thyroiditis [see Warnings and Precautions (5.1)].
- Radiation-induced Toxicities [see Warnings and Precautions (5.2)].
- Hypersensitivity Reactions [see Warnings and Precautions (5.3)].
- Embryo-Fetal Toxicity [see Warnings and Precautions (5.4), Use in Specific Populations (8.1)].
- Increased Radiation Exposure to Breast Tissue with Lactation [see Warnings and Precautions (5.5), Use in Specific Populations (8.2)].
- Transient Infertility [see Warnings and Precautions (5.6), Use in Specific Populations (8.3)].
- Radiation Exposure to Other Individuals [see Warnings and Precautions (5.7)].
- Risk of Decreased Effectiveness of Therapy [see Warnings and Precautions (5.8)].

6.1 Postmarketing Experience

The following adverse reactions have been reported during post-approval use of sodium iodide I 131 (Table 3). Because these reactions are reported voluntarily from a population of uncertain size, it is not always possible to reliably estimate their frequency or establish a causal relationship to drug exposure.

Table 3 Postmarket Adverse Reactions by System Organ Class
System Organ Class [In alphabetical order] | Symptoms
Cardiac disorders | Chest pain, tachycardia
Congenital, familial and genetic disorders | Chromosomal abnormalities, congenital hypothyroidism
Endocrine disorders | Hyperthyroidism, hypoparathyroidism, hypothyroidism, thyrotoxic crisis
Eye disorders | Lacrimal gland dysfunction
Gastrointestinal disorders | Gastritis, nausea, salivary gland dysfunction, sialadenitis, vomiting
General disorders and administration site conditions | Local swelling of thyroid or sites of iodide avid tumor
Hematologic and lymphatic disorders including fatalities | Anemia, blood dyscrasia, bone marrow depression, leukopenia, thrombocytopenia
Immune system disorders | Bronchospasm
Neoplasms benign, malignant and unspecified (including cysts and polyps) | Acute leukemia, solid cancer
Nervous system disorders | [In patients with iodide-avid brain metastases] Cerebral edema, headache
Respiratory, thoracic and mediastinal disorders | [In patients with iodide-avid lung metastases] Pulmonary fibrosis, radiation pneumonitis
Skin and subcutaneous tissue disorders | Hives, itching, rash

7 DRUG INTERACTIONS

- Concomitant use of bone marrow depressants may enhance the depression of the hematopoietic system caused by the use of large doses of sodium iodide I 131 [see Warnings and Precautions (5.2)].
- Many drugs and iodide-containing foods interfere with the accumulation of radioiodide by the thyroid. Review the patient’s history, current medications, and recent diagnostic tests prior to the administration of sodium iodide I 131 [see Warnings and Precautions (5.8)].
- Advise patients to maintain a low-iodide diet two weeks prior to radioiodide administration and continue for several days during the uptake or imaging process and to discontinue taking the following products before they undergo the procedure as shown in Table 4.

Table 4 Pharmaceuticals / OTCs / Agents Blocking Radioiodine Uptake
Type of Medication | Recommended time of withdrawal
Thionamide medications (e.g., propylthiouracil, methimazole, carbimazole) | 3 days
Multivitamins containing iodide | 10 days
Natural or synthetic thyroid hormones triiodothyronine thyroxine | 2 weeks 4 weeks
Iodide-containing foods: iodized salt, dairy products, egg yolks, seafood, turkey and liver | 2 weeks
Kelp, agar, carrageenan, Lugol solution | 3 weeks
Saturated solution of potassium iodide | 3 weeks
Topical iodide (e.g., surgical skin preparation) | 3 weeks
Intravenous radiographic contrast agents Water soluble Lipophilic | 2 months 6 months
Amiodarone | 6 months

8 USE IN SPECIFIC POPULATIONS

8.1 Pregnancy

Risk Summary
HICON® is contraindicated in pregnancy because fetal exposure can lead to neonatal hypothyroidism, which in some cases is severe and irreversible [See Warnings and Precautions (5.4)]. Data from the published literature describe reports of neonatal thyroid abnormalities after fetal exposure; including agenesis of the thyroid and hypothyroidism (see Clinical Considerations, Data). No animal reproductive studies have been conducted.

Clinical Considerations
Fetal/ Neonatal Adverse Reactions
A fetus exposed to sodium iodide I 131 can develop neonatal hypothyroidism. Delay in diagnosis of neonatal hypothyroidism after exposure to sodium iodide I 131 in utero can result in severe sequelae such as cognitive impairment and delayed bone age. Monitor thyroid function in any infant born after in utero exposure to sodium iodide I 131.

Data
Human Data
Sodium iodide I 131 crosses the placenta and the fetal thyroid begins to concentrate iodide during the 10th to 12th week of gestation. In literature reports of maternal exposures to sodium iodide I 131 at doses of 333 MBq to 8,325 MBq (9 mCi to 225 mCi) during 4 to 26 weeks gestational age, the most common adverse outcomes were hypothyroid infants and children.

8.2 Lactation

Risk Summary
HICON® is contraindicated during lactation because I 131 concentrates in the breast during lactation via the increased expression of the sodium iodide symporter in breast tissue and can lead to hypothyroidism in the infant through breastfeeding. If sodium iodide I 131 is administered postpartum, breastfeeding should not be restarted for the remainder of the postpartum period. In addition, to minimize the absorbed radiation dose to the breast tissue, breastfeeding and breast-pumping should be discontinued for at least 6 weeks before administration of sodium iodide I 131 [see Data and Warnings and Precautions (5.5)].

Infants exposed to sodium iodide I 131 through breast milk are at risk for development of hypothyroidism because sodium iodide I 131 is distributed into breast milk and may reach concentrations equal to or greater than concentrations in maternal plasma (see Data).

Data
Published literature describes sodium iodide I 131 transfer into breast milk and uptake by the thyroid of the breastfed infant. The amount of sodium Iodide I 131 detected in the breast milk at 36 to 48 hours after administration is 1% to 27% of the injected dose (with injected doses between 1.1 MBq (0,0297 mCi) to 5,143 MBq (139 mCi)).

8.3 Female and Males of Reproductive Potential

HICON® is contraindicated in pregnancy because of the risk of fetal hypothyroidism [see Warnings and Precautions (5.4) and Use in Specific Populations (8.1)].

Pregnancy Testing
Obtain a pregnancy test in females of reproductive potential and verify the absence of pregnancy within 24 hours prior to administration of treatment [see Dosage and Administration (2.2)].

Contraception
Advise females and males of reproductive potential to use effective contraception during treatment with HICON® and for at least six months after the last dose of HICON®.

Infertility
Females
Fertility may be impaired with HICON® treatment. Transient amenorrhea and ovarian insufficiency have been observed after sodium iodide I 131 therapy in females. The literature describes reports of transient menstrual cycle irregularities, including amenorrhea, and ovarian failure in females treated with cumulative doses of 1,000 MBq to 59,000 MBq (27 mCi to 1,595 mCi) sodium iodide I 131. In a published literature analysis, the effects on fertility occurred in up to 30% of women treated with sodium iodide I 131, and may resolve 12 months after treatment.

Males
Fertility may be impaired with HICON® treatment. Discuss sperm banking for males who are expected to receive a high cumulative dose of sodium iodide I 131. Transient dose-related impairment of testicular function after sodium iodide I 131 therapy has been reported in the published literature. The literature describes reports of males treated with sodium iodide I 131 at doses of 370 MBq to 22,000 MBq (10 mCi to 595 mCi) resulting in transiently impaired testicular function (including spermatogenesis). The risk of persistent testicular dysfunction increases after administration of repeated or high cumulative radioiodide exposure.

8.4 Pediatric Use

The safety and effectiveness of HICON® have not been established in pediatric patients. Pediatric patients are at an increased lifetime risk for malignancy from radiation exposure.

8.5 Geriatric Use

Clinical experience has not identified differences in safety or effectiveness in geriatric patients compared to younger patients. However, elderly patients are more likely to have decreased renal function and radiation exposure is greater in patients with impaired renal function [see Use in Specific Populations (8.6), Clinical Pharmacology (12.3)].

8.6 Renal Impairment

HICON® is primarily excreted by the kidneys. Renal function impairment decreases excretion of sodium iodide I 131 and increases the radiation exposure and risk of radiation toxicity. For patients with a history of renal impairment, evaluate renal function for therapeutic planning and consider dosimetry. Sodium Iodide I 131 is dialyzable. Hemodialysis can be used to reduce total body radiation exposure [see Clinical Pharmacology (12.3)].

10 OVERDOSAGE

In case of exposure to a radioactive dose of sodium iodide I 131 exceeding the intended therapeutic dose, provide general supportive care, promote frequent voiding, monitor for bone marrow and thyroid suppression. Consider administering a thyroid blocking agent (e.g. potassium iodide (KI) or perchlorate) promptly within 4 to 6 hours after the exposure. Assess the benefit of administering a thyroid blocking agent against the risk of failure of sodium iodide I 131 therapy. Appropriate replacement therapy is recommended if hypothyroidism occurs.

11 DESCRIPTION

11.1 Chemical Characteristics

HICON®, a radioactive therapeutic agent, provides a concentrated solution of sodium iodide I 131 with a radioconcentration of 37,000 MBq/mL (1,000 mCi/mL). Each mL of the concentrated solution contains 37,000 MBq (1,000 mCi) of no-carrier-added sodium iodide I 131, disodium edetate dihydrate USP as a stabilizer, sodium thiosulfate pentahydrate USP as a reducing agent, and dibasic sodium phosphate anhydrous USP. The pH of the concentrated solution is between 7.5 and 10.

The concentrated solution provided with HICON® is used for the preparation of sodium iodide I 131 capsules or sodium iodide I 131 solution of varying strengths for oral administration for therapy.

Sodium iodide I 131 solution is designated chemically as Na ^131I and has a molecular weight of 153.99 g/mol. Hard gelatin capsules, provided for the preparation of the sodium iodide I 131 capsules final dosage form, contain approximately 300 mg of dibasic sodium phosphate anhydrous USP as the absorbing buffer.

11.2 Physical Characteristics

Iodide I 131 decays by beta emission and associated gamma emission with a physical half-life of 8.02 days. The principal radiation emissions are listed in Table 5.

Table 5 Principal Radiation Emission Data from Decay of Sodium Iodide I 131
Radiation | Mean % per Disintegration | Mean Energy (keV)
Beta-1 | 2.1% | 69.4
Beta-3 | 7.2% | 96.6
Beta-4 | 89.4% | 191.6
Gamma-7 | 6.1% | 284.3
Gamma-14 | 81.2% | 364.5
Gamma-18 | 7.1% | 637.0

11.3 External Radiation

The specific gamma-ray constant for iodide I 131 is 4.26 × 10^-13 C•m^2•kg^-1•MBq^-1•s^-1 (2.2 R•cm^2/mCi•hr). The first half-value thickness of lead (Pb) for iodide I 131 is 0.27 cm. A range of values for the relative attenuation of the radiation emitted by iodide I 131 that results from interposition of various thicknesses of Pb is shown in Table 6. For example, the use of 2.59 cm of Pb will decrease the external radiation exposure by a factor of about 100.

Table 6 Radiation Attenuation of Iodine I 131 by Lead Shielding
Shield Thickness (Pb) cm | Coefficient of Attenuation
0.27 | 0.5
0.56 | 0.25
0.99 | 10^-1
2.59 | 10^-2
4.53 | 10^-3

To correct for physical decay of iodine I 131, the fractions that remain at selected intervals after the time of calibration are shown in Table 7.

Table 7 Physical Decay Chart: Iodine I-131 Half-Life 8.02 Days
Days | Fraction Remaining | Days | Fraction Remaining | Days | Fraction Remaining
0 [Calibration time] | 1.000 | 11 | 0.388 | 22 | 0.151
1 | 0.918 | 12 | 0.356 | 23 | 0.138
2 | 0.842 | 13 | 0.327 | 24 | 0.127
3 | 0.773 | 14 | 0.300 | 25 | 0.116
4 | 0.709 | 15 | 0.275 | 26 | 0.107
5 | 0.651 | 16 | 0.253 | 27 | 0.098
6 | 0.597 | 17 | 0.232 | 28 | 0.090
7 | 0.548 | 18 | 0.213 | 29 | 0.083
8 | 0.503 | 19 | 0.195 | 30 | 0.076
9 | 0.461 | 20 | 0.179
10 | 0.423 | 21 | 0.164

12 CLINICAL PHARMACOLOGY

12.1 Mechanism of Action

Iodide is actively transported by the sodium-iodide symporter (NIS) protein, in thyroid follicular cells. Iodide is concentrated in follicular cells to levels up to 50 times higher than in the plasma. Iodide is metabolically oxidized by thyroid peroxidase to iodinium (I^+) which in turn iodinates tyrosine residues of thyroglobulin (tri or tetra-iodinated tyrosine). The beta emission of I 131 is responsible for the therapeutic effect.

12.2 Pharmacodynamics

The relationship between the extent of iodide I 131 exposure and pharmacologic effects has not been explored in clinical trials.

12.3 Pharmacokinetics

Absorption
Following oral administration of HICON®, 90% of the administered radioactivity of sodium iodide I 131 is systemically absorbed in the first 60 minutes.

Distribution
Following absorption, sodium iodide I 131 is distributed within the extra-cellular space. It is actively transported by the sodium-iodide symporter (NIS) protein, and binds to thyroglobulin resulting in accumulation in the thyroid. The thyroid uptake of iodide is usually increased in hyperthyroidism and in goiter, and is decreased in hypothyroidism. Sodium iodide I 131 also accumulates in the stomach, choroid plexus, salivary glands, breast, liver, gall bladder, and kidneys.

Elimination
Metabolism
In thyroidal follicular cells iodide is oxidized through the action of thyroid peroxidase to iodinium (I^+) which in turn iodinates tyrosine residues of thyroglobulin.

Excretion
Sodium iodide I 131 is excreted in urine and feces. The normal range of urinary excretion is 37% to 75% of the administered dose, varying with the thyroid and renal function of the patient. Fecal excretion is about 10%.

16 HOW SUPPLIED/STORAGE AND HANDLING

16.1 How Supplied

HICON® provides a concentrated solution of sodium iodide I 131 with a radioconcentration of 37,000 MBq/mL (1,000 mCi/mL). It is supplied in 1 mL clear vials that contain approximately 9,250 MBq (250 mCi), 18,500 MBq (500 mCi), and 37,000 MBq (1,000 mCi) at the time of calibration.

The concentrated solution is intended for use in the preparation of capsules and solutions of varying strengths for oral administration.

HICON®
NDC | Volume of Concentrated Solution | Total Radioactivity per Vial
65174-880-25 | 0.25 mL | 9,250 MBq (250 mCi)
65174-880-50 | 0.50 mL | 18,500 MBq (500 mCi)
65174-880-00 | 1 mL | 37,000 MBq (1,000 mCi)

A minimum of one blister package of 10 empty large hard gelatin capsules and a minimum of one blister package of 10 small hard gelatin capsules containing approximately 300 mg of dibasic sodium phosphate anhydrous as the absorbing buffer are supplied along with HICON® for the preparation of sodium iodide I 131 capsules, therapeutic.

16.2 Storage and Handling

HICON® should be stored between 2 °C and 25 °C (36 °F and 77 °F). Store and dispose of HICON® in compliance with the appropriate regulations of the government agency authorized to license the use of this radionuclide. Use HICON® solution per the expiry date on the lead pot label. Use prepared capsules within 7 days of preparing.

Discard unused capsules after all HICON® solution has been dispensed or expired. New blister packages of hard gelatin capsules are provided with each new shipment of HICON®.

This radiopharmaceutical is approved for use by persons under license by the Nuclear Regulatory Commission or the relevant regulatory authority of an Agreement State.

17 PATIENT COUNSELING INFORMATION

Radiation Safety Precautions

- Advise patients treated for hyperthyroidism to monitor for and seek medical care for signs and symptoms of
  thyrotoxicosis and thyroid storm arising during the post-treatment period. For mild radiation-induced thyroiditis, patients may be advised to consider symptomatic management with pain-relievers or anti-inflammatory medications [see Warnings and Precautions (5.1)].
- Advise patients to hydrate and void frequently and to use a sialagogue after administration of radioiodide to minimize radiation dose [see Warnings and Precautions (5.2)].
- Advise patients to avoid close contact with others, especially pregnant women and children, and to take care to avoid contamination of other persons or the environment with body fluids [see Warnings and Precautions (5.7)].

Embryo-Fetal Toxicity

- Advise female patients of the risk to a fetus [see Warnings and Precautions (5.4), Use in Specific Populations (8.1)].
- Advise females and males of reproductive potential to use effective contraception during treatment with HICON® and for at least 6 months after the last dose [see Warnings and Precautions (5.4), Use in Specific Populations (8.3)].
- Advise female patients to contact their healthcare provider with a known or suspected pregnancy.

Lactation

- Instruct women to stop breastfeeding and breast-pumping for the remainder of the postpartum period after and for at least 6 weeks prior to HICON® administration [see Contraindications (4), Warnings and Precautions (5.5), Use in Specific Populations (8.2)].

Effects on Fertility

- Advise females and males of reproductive potential of the potential for impaired fertility with HICON® treatment and possible use of sperm banking for males of reproductive potential [see Warnings and Precautions (5.6), Use in Specific Populations (8.3)]

Manufactured by:

Jubilant DraxImage Inc., dba Jubilant RadiopharmaTM
16 751 TransCanada Highway
Kirkland, Quebec H9H 4J4 Canada
1-888-633-5343
www.jubilantradiopharma.com

Revised: November 2021

Art Rev.: 2.1

50000000796

HICON® is a registered trademark of Jubilant DraxImage Inc.

Jubilant RadiopharmaTM is a trademark used under license by Jubilant DraxImage Inc.